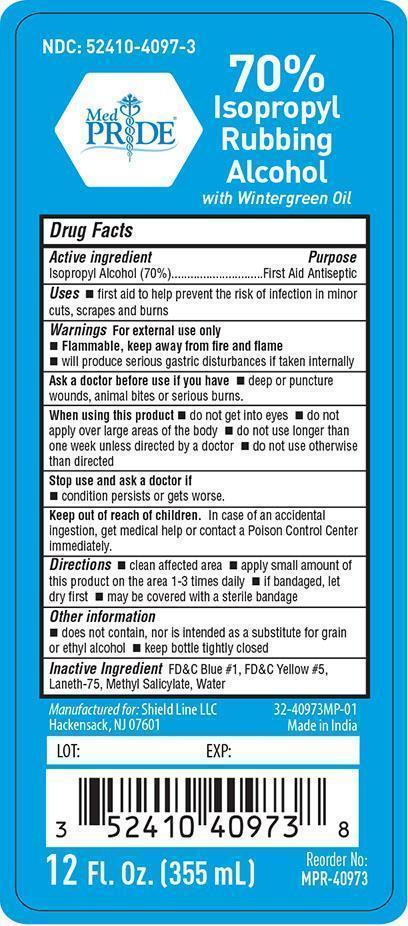 DRUG LABEL: MedPRIDE
NDC: 52410-4097 | Form: LIQUID
Manufacturer: Shield Line LLC
Category: otc | Type: HUMAN OTC DRUG LABEL
Date: 20240417

ACTIVE INGREDIENTS: ISOPROPYL ALCOHOL 70 mL/100 mL
INACTIVE INGREDIENTS: FD&C BLUE NO. 1; FD&C YELLOW NO. 5; METHYL SALICYLATE; WATER

MedPride 70% Rubbing Alcohol Wintergreen

Active ingredient

Isopropyl Alcohol 70%

Purpose

First Aid Antiseptic

Uses

■ first aid to help prevent risk of infection in minor cuts, scrapes and burns

Warnings

For external use only

■ Flammable, keep away from fire and flame

■ will produce serious gastric disturbances if taken internally

Ask a doctor before use if you have

■ deep or puncture wounds, animal bites or serious burns

When using this product

■ do not get into eyes ■ do not apply over large areas of the body ■ do not use longer than one week unless directed by a doctor

■ do not use otherwise than directed

Stop use and ask a doctor if

■ condition persists or gets worse

Keep out of reach of children

In case of an accidental ingestion, get medical help or contact a Poison Control Center immediately

Directions

■ clean affected area ■ apply small amount of this product on the area 1 to 3 times daily

■ if bandaged, let dry first ■ may be covered with a sterile bandage

Other information

■ does not contain, nor is intended as a substitute for grain or ethyl alcohol ■ keep bottle tightly closed

Inactive Ingredient

FDC Blue 1, FDC Yellow 5, Laneth-75, Methyl Salicylate, Water